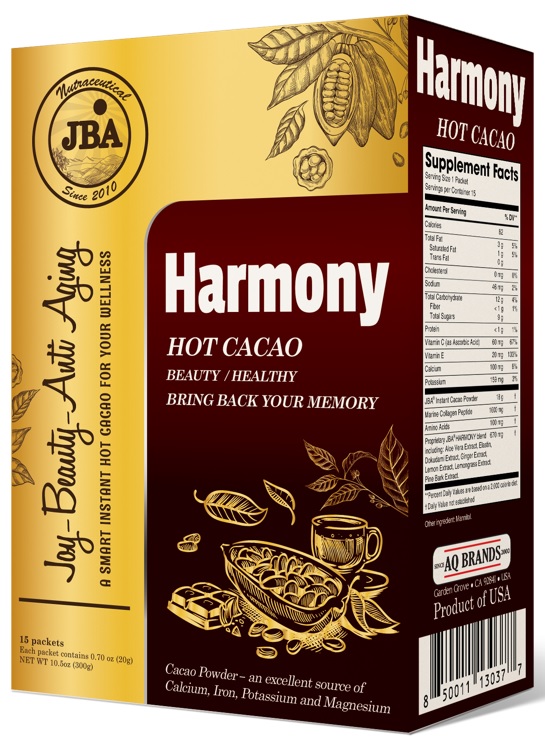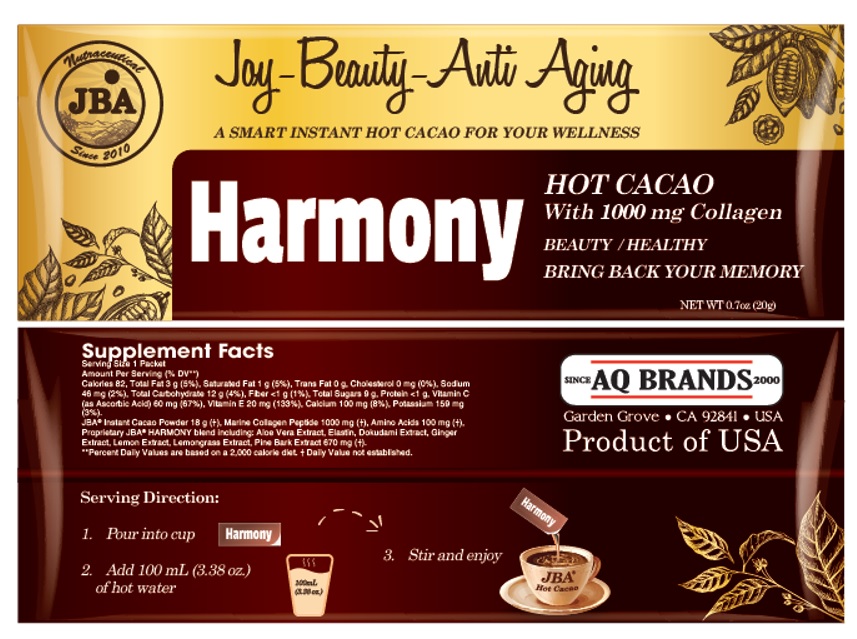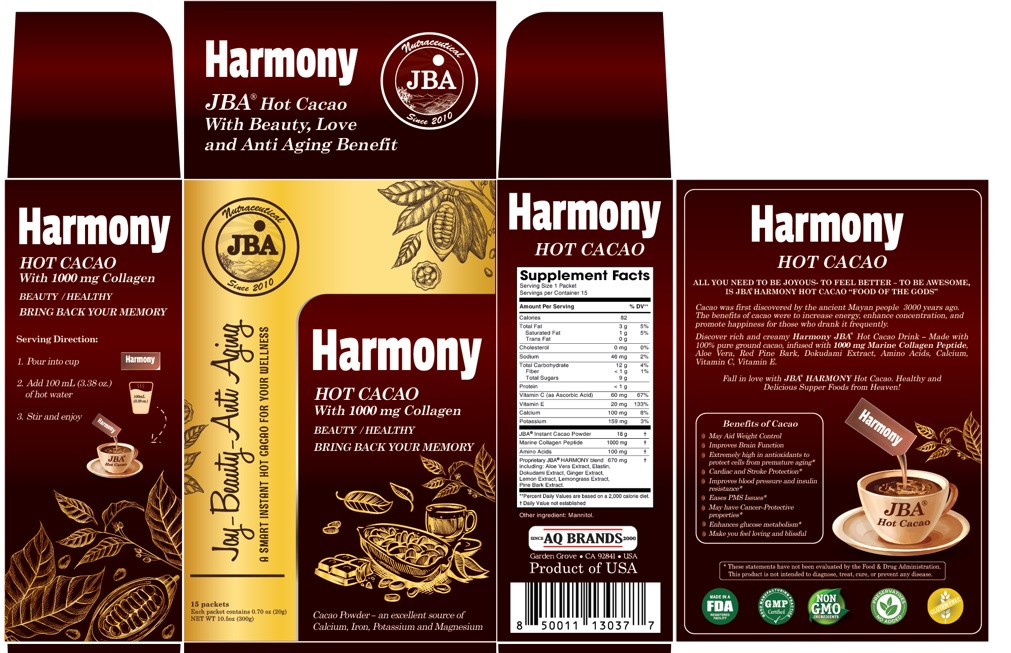 DRUG LABEL: JBA Harmony Hot Cacao with 1000 mg Collagen
NDC: 13411-879 | Form: POWDER
Manufacturer: Advanced Pharmaceutical Services, Inc. Dba Affordable Quality Pharmaceuticals
Category: other | Type: DIETARY SUPPLEMENT
Date: 20210913

ACTIVE INGREDIENTS: .ALPHA.-TOCOPHEROL 20 mg/20 g; ASCORBIC ACID 60 mg/20 g; POTASSIUM 159 mg/20 g; CALCIUM 100 mg/20 g; MARINE COLLAGEN, SOLUBLE 1000 mg/20 g; COCOA 18 g/20 g; AMINO ACIDS, SOURCE UNSPECIFIED 100 mg/20 g; ALOE VERA LEAF 200 mg/20 g; ELASTIN BOVINE 10 mg/20 g; GINGER 35 mg/20 g; HOUTTUYNIA CORDATA TOP 300 mg/20 g; LEMON 35 mg/20 g; CYMBOPOGON CITRATUS LEAF 30 mg/20 g; MARITIME PINE 60 mg/20 g
INACTIVE INGREDIENTS: MANNITOL

Identity

Dietary supplement

Direction

1. Pour into cup
2. Add 100 mL (3.38 oz.) of hot water
3. Stir and enjoy.

Safe handling warning

JBA® Harmony Hot Cacao With Beauty, Love and Anti Aging Benefit

JBA® Harmony Hot Cacao With 1000 mg Collagen
BEAUTY / HEALTHY
BRING BACK YOUR MEMORY

Cacao Powder - an excellent source of Calcium, Iron, Potassium and Magnesium

ALL YOU NEED TO BE JOYOUS- TO FEEL BETTER - TO BE AWESOME, IS JBA HARMONY HOT CACAO “FOOD OF THE GODS”
Cacao was first discovered by the ancient Mayan people 3000 years ago. The benefits of cacao were to increase energy, enhance concentration, and promote happiness for those who drank it frequently.
Discover rich and creamy Harmony JBA Hot Cacao Drink -
Made with 100% pure ground cacao, infused with 1000 mg Marine Collagen Peptide Aloe Vera, Red Pine Bark, Dokudami Extract, Amino Acids, Calcium, Vitamin C, Vitamin E.
Fall in love with JBA HARMONY Hot Cacao. Healthy and Delicious Supper Foods from Heaven!

HEALTH CLAIM

Benefits of Cacao
- May Aid Weight Control
- Improves Brain Function
- Extremely high in antioxidants to protect cells from premature aging*
- Cardiac and Stroke Protection*
- Improves blood pressure and insulin resistance*
- Eases PMS Issues*
- May have Cancer-Protective properties*
- Enhances glucose metabolism*
- Make you feel loving and blissful
* These statements have not been evaluated by the Food & Drug Administration. This product is not intended to diagnose, treat, cure, or prevent any disease.